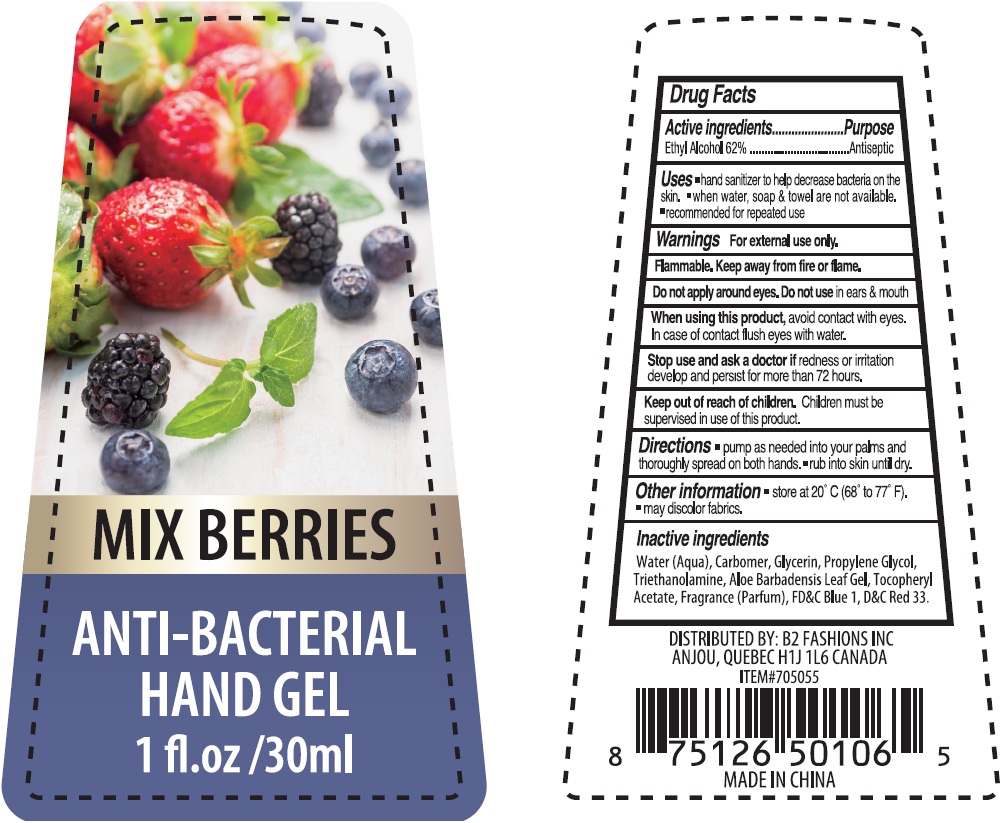 DRUG LABEL: Mix Berries Anti Bacterial Hand Sanitizer
NDC: 71372-003 | Form: GEL
Manufacturer: B2 Fashions Inc.
Category: otc | Type: HUMAN OTC DRUG LABEL
Date: 20170405

ACTIVE INGREDIENTS: ALCOHOL 620 mg/1 mL
INACTIVE INGREDIENTS: WATER; CARBOXYPOLYMETHYLENE; GLYCERIN; PROPYLENE GLYCOL; TROLAMINE; .ALPHA.-TOCOPHEROL ACETATE; FD&C BLUE NO. 1; D&C RED NO. 33

Mix Berries Anti-Bacterial Hand Sanitizer

Active ingredients

Ethyl Alcohol 62%

Purpose

Antiseptic

Uses

- hand sanitizer to help decrease bacteria on the skin.
- When water, soap & towel are not available.
- recommended for repeated use

Warnings

For external use only.

Flammable. Keep away from fire or flame.

Do not apply around eyes.

Do not use

in ears & mouth

When using this product,

avoid contact with eyes. In case of contact flush eyes with water.

Stop use and ask a doctor if

redness or irritation develop and persist for more than 72 hours.

Keep out of reach of children.

Children must be supervised in use of this product.

Directions

- pump as needed into your palms and thoroughly spread on both hands.
- rub into skin until dry.

Other information

- store at 20° C (68° to 77° F).
- may discolor fabrics.

Inactive ingredients

Water (Aqua), Carbomer, Glycerin, Propylene Glycol, Triethanolamine, Aloe Barbadensis Leaf Gel, Tocopheryl Acetate, Fragrance (Parfum), FD&C Blue 1, D&C Red 33.